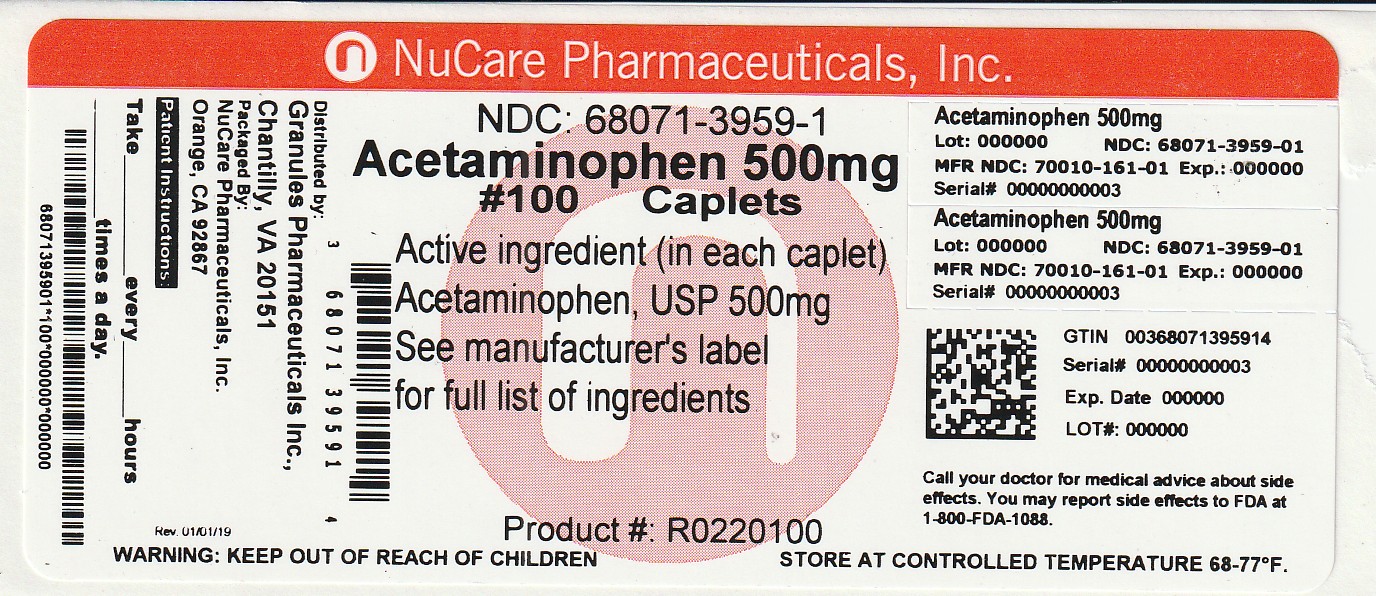 DRUG LABEL: ACETAMINOPHEN
NDC: 68071-3959 | Form: TABLET
Manufacturer: NuCare Pharmaceuticals, Inc.
Category: otc | Type: HUMAN OTC DRUG LABEL
Date: 20260127

ACTIVE INGREDIENTS: ACETAMINOPHEN 500 mg/1 1
INACTIVE INGREDIENTS: POVIDONE K30; STARCH, CORN; STEARIC ACID; SODIUM STARCH GLYCOLATE TYPE A POTATO; HYPROMELLOSE, UNSPECIFIED; POLYETHYLENE GLYCOL 400

Acetaminophen Tablets 500 mg

ACTIVE INGREDIENT (IN EACH CAPLET)

Acetaminophen, USP 500 mg

PURPOSE

Pain reliever/fever reducer

USES

• temporarily relieves minor aches and pains due to:
• the common cold
• headache

• backache

• minor pain of arthritis

• toothache
• muscular aches
• premenstrual and menstrual cramps
• temporarily reduces fever

WARNINGS

Liver warning:This product contains acetaminophen. Severe Liver damage may occur if you take
• more than 4,000 mg of acetaminophen 24 hours.

• with other drugs containing acetaminophen
• 3 or more alcoholic drinks everyday while using this product

Allergy alert:acetaminophen may cause severe skin reactions.Symptoms may include:
• skin reddening
• blisters
• rash
If a skin reaction occurs, stop use and seek medical help right away.

Do not use

• with any other drugs containing acetaminophen (prescription or nonprescription). If you are not sure whether a drug contains acetaminophen, ask a doctor or pharmacist.
• if you are allergic to acetaminophen or any other inactive ingredients in this product.

Ask a doctor before use if you have

liver disease.

Ask a doctor or pharmacist before use if you are

taking the blood thinning drug warfarin.

Stop use and ask doctor if

• pain gets worse or lasts more than 10 days
• fever gets worse or lasts more than 3 days
• new symptoms occur
• redness or swelling is present
These could be signs of a serious condition.

If pregnant or breast-feeding

ask a health professional before use.

Keep out of reach of children

Over dose warning: In case of overdose, get medical help or Contact Poison Control Center right away. (1-800-222-1222) Quick medical attention is critical for adults as well as for children even if you do not notice any signs or symptoms.

DIRECTIONS

• do not take more than directed (see overdose warning)

adults and children 12 years and over | • take 2 caplets every 6 hours while symptoms last • do not take more than 6 caplets in 24 hours, unless directed by a doctor • do not use for more than 10 days unless directed by a doctor
children under 12 years | • ask a doctor

OTHER INFORMATION

•store at 20-25°C (68-77°F). See USP Controlled Room Temparature

•avoid high humidity

•See end panel for lot number and expiration date

INACTIVE INGREDIENTS

hydroxyethyl methyl cellulose, polyethylene glycol, povidone, pregelatinized starch, sodium starch glycolate, stearic acid.

QUESTIONS OR COMMENTS ?

Contact 1-877-770-3183Mon-Fri 8:00 AM EST to 5:00 PM PST.

+All trademarkes are property of their reapective owners.

This product is not affliated with the makers/owners of

Extra Strength Tylenol®Caplets.

Distributed by:

Granules Pharmaceuticals INc.,

Chantilly, VA 20151

MADE IN INDIA

Rev.08/21